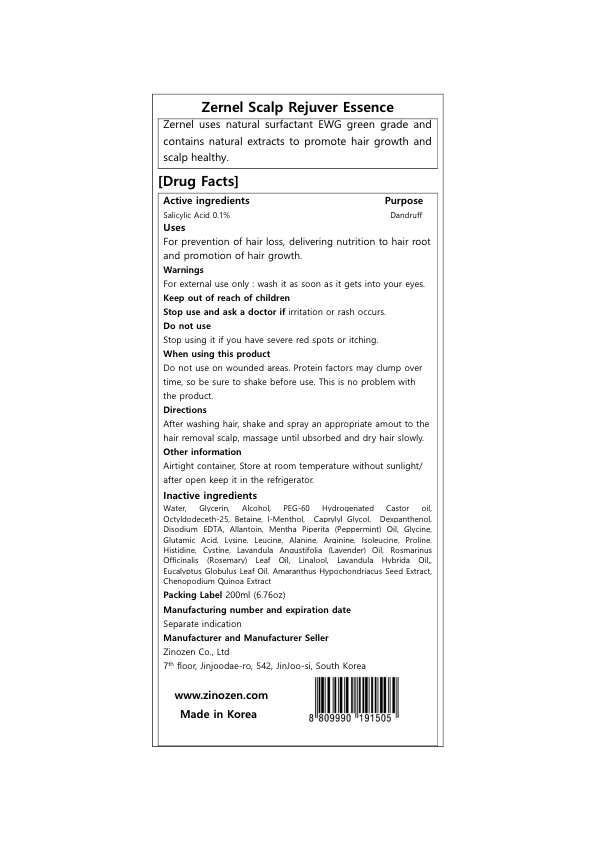 DRUG LABEL: Zernel Scalp Rejuver Essence
NDC: 80152-302 | Form: LIQUID
Manufacturer: ZINOZEN CO., LTD.
Category: otc | Type: HUMAN OTC DRUG LABEL
Date: 20210323

ACTIVE INGREDIENTS: SALICYLIC ACID 0.1 mg/100 mL
INACTIVE INGREDIENTS: ALANINE; ISOLEUCINE; LAVENDER OIL; DEXPANTHENOL; AMARANTHUS HYPOCHONDRIACUS SEED; PEPPERMINT OIL; GLYCINE; PROLINE; HISTIDINE; CYSTINE; LINALOOL, (+/-)-; EUCALYPTUS OIL; WATER; PEG-60 HYDROGENATED CASTOR OIL; OCTYLDODECETH-25; LEVOMENTHOL; CAPRYLYL GLYCOL; EDETATE DISODIUM ANHYDROUS; ALLANTOIN; ALCOHOL; GLYCERIN; BETAINE; CHENOPODIUM QUINOA SEED; GLUTAMIC ACID; LYSINE; LEUCINE; ARGININE; ROSEMARY OIL; LAVANDIN OIL

80152-303 SCALP REJUVER ESSENCE

Active ingredients

Salicylic Acid 0.1%

Purpose

Dandruff

Uses

For prevention of hair loss, delivering nutrition to hair root and promotion of hair growth.

Warnings

For external use only : wash it as soon as it gets into your eyes.

Keep out of reach of children

Stop use and ask a doctor if

irritation or rash occurs.

Do not use

Stop using it if you have severe red spots or itching.

When using this product

Do not use on wounded areas. Protein factors may clump over time, so be sure to shake before use. This is no problem with the product.

Directions

After washing hair, shake and spray an appropriate amout to the hair removal scalp, massage until ubsorbed and dry hair slowly.

Other information

Airtight container, Store at room temperature without sunlight/ after open keep it in the refrigerator.

Inactive ingredients

Water, Glycerin, Alcohol, PEG-60 Hydrogenated Castor oil, Octyldodeceth-25, Betaine, l-Menthol, Caprylyl Glycol, Dexpanthenol, Disodium EDTA, Allantoin, Mentha Piperita (Peppermint) Oil, Glycine, Glutamic Acid, Lysine, Leucine, Alanine, Arginine, Isoleucine, Proline, Histidine, Cystine, Lavandula Angustifolia (Lavender) Oil, Rosmarinus Officinalis (Rosemary) Leaf Oil, Linalool, Lavandula Hybrida Oil,, Eucalyptus Globulus Leaf Oil, Amaranthus Hypochondriacus Seed Extract, Chenopodium Quinoa Extract